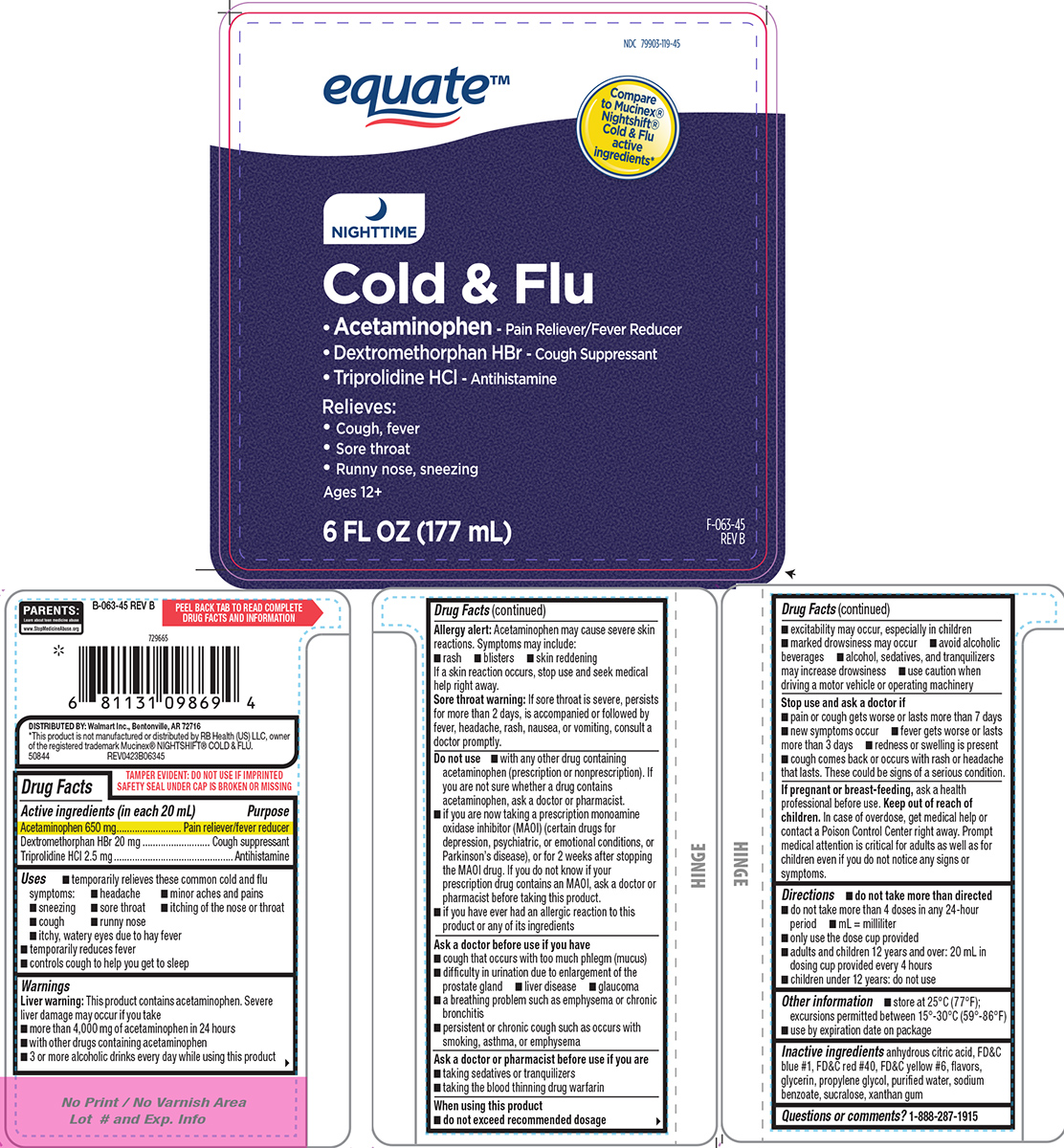 DRUG LABEL: Cold and Flu
NDC: 79903-119 | Form: SOLUTION
Manufacturer: WALMART INC.
Category: otc | Type: HUMAN OTC DRUG LABEL
Date: 20251212

ACTIVE INGREDIENTS: ACETAMINOPHEN 650 mg/20 mL; DEXTROMETHORPHAN HYDROBROMIDE 20 mg/20 mL; TRIPROLIDINE HYDROCHLORIDE 2.5 mg/20 mL
INACTIVE INGREDIENTS: ANHYDROUS CITRIC ACID; FD&C BLUE NO. 1; FD&C RED NO. 40; FD&C YELLOW NO. 6; GLYCERIN; PROPYLENE GLYCOL; WATER; SODIUM BENZOATE; SUCRALOSE; XANTHAN GUM

Equate 44-063

Active ingredients (in each 20 mL)

Acetaminophen 650 mg
Dextromethorphan HBr 20 mg
Triprolidine HCl 2.5 mg

Purpose

Pain reliever/fever reducer
Cough suppressant
Antihistamine

Uses

- temporarily relieves these common cold and flu symptoms:
  - cough
  - headache
  - runny nose
  - sneezing
  - sore throat
  - itching of the nose or throat
  - minor aches and pains
  - itchy, watery eyes due to hay fever
- temporarily reduces fever
- controls cough to help you get to sleep

Warnings

Liver warning: This product contains acetaminophen. Severe liver damage may occur if you take

- more than 4,000 mg of acetaminophen in 24 hours
- with other drugs containing acetaminophen
- 3 or more alcoholic drinks every day while using this product

Allergy alert: Acetaminophen may cause severe skin reactions. Symptoms may include:

- rash
- blisters
- skin reddening

If a skin reaction occurs, stop use and seek medical help right away.

Sore throat warning: If sore throat is severe, persists for more than 2 days, is accompanied or followed by fever, headache, rash, nausea, or vomiting, consult a doctor promptly.

Do not use

- with any other drug containing acetaminophen (prescription or nonprescription). If you are not sure whether a drug contains acetaminophen, ask a doctor or pharmacist.
- if you have ever had an allergic reaction to this product or any of its ingredients
- if you are now taking a prescription monoamine oxidase inhibitor (MAOI) (certain drugs for depression, psychiatric, or emotional conditions, or Parkinson’s disease), or for 2 weeks after stopping the MAOI drug. If you do not know if your prescription drug contains an MAOI, ask a doctor or pharmacist before taking this product.

Ask a doctor before use if you have

- liver disease
- glaucoma
- cough that occurs with too much phlegm (mucus)
- difficulty in urination due to enlargement of the prostate gland
- a breathing problem such as emphysema or chronic bronchitis
- persistent or chronic cough such as occurs with smoking, asthma, or emphysema

Ask a doctor or pharmacist before use if you are

- taking sedatives or tranquilizers
- taking the blood thinning drug warfarin

When using this product

- do not exceed recommended dosage
- excitability may occur, especially in children
- avoid alcoholic beverages
- marked drowsiness may occur
- alcohol, sedatives, and tranquilizers may increase drowsiness
- use caution when driving a motor vehicle or operating machinery

Stop use and ask a doctor if

- pain or cough gets worse or lasts more than 7 days
- fever gets worse or lasts more than 3 days
- new symptoms occur
- redness or swelling is present
- cough comes back or occurs with rash or headache that lasts. These could be signs of a serious condition.

If pregnant or breast-feeding,

ask a health professional before use.

Keep out of reach of children.

In case of overdose, get medical help or contact a Poison Control Center right away. Prompt medical attention is critical for adults as well as for children even if you do not notice any signs or symptoms.

Directions

- do not take more than directed
- do not take more than 4 doses in any 24-hour period
- mL = milliliter
- only use the dose cup provided
- adults and children 12 years and over: 20 mL in dosing cup provided every 4 hours
- children under 12 years: do not use

Other information

- store at 25°C (77°F); excursions permitted between 15°-30°C (59°-86°F)
- use by expiration date on package

Inactive ingredients

anhydrous citric acid, FD&C blue #1, FD&C red #40, FD&C yellow #6, flavors, glycerin, propylene glycol, purified water, sodium benzoate, sucralose, xanthan gum

Questions or comments?

1-888-287-1915

Principal display panel

equate™

NDC 79903-119-45

Compare to Mucinex® Nightshift® Cold & Flu active ingredients*

NIGHTTIME

Cold & Flu

• Acetaminophen - Pain Reliever/Fever Reducer
• Dextromethorphan HBr - Cough Suppressant
• Triprolidine HCl - Antihistamine

Relieves:
• Cough, fever
• Sore throat
• Runny nose, sneezing

Ages 12+

6 FL OZ (177 mL) F-063-45 REVB

PARENTS:
Learn about teen medicine abuse
www.StopMedicineAbuse.org

TAMPER EVIDENT: DO NOT USE IF IMPRINTED
SAFETY SEAL UNDER CAP IS BROKEN OR MISSING

DISTRIBUTED BY: Walmart Inc., Bentonville, AR 72716
*This product is not manufactured or distributed by RB Health (US) LLC, owner
of the registered trademark Mucinex® NIGHTSHIFT® COLD & FLU.
50844 REV0423B06345

Equate 44-063